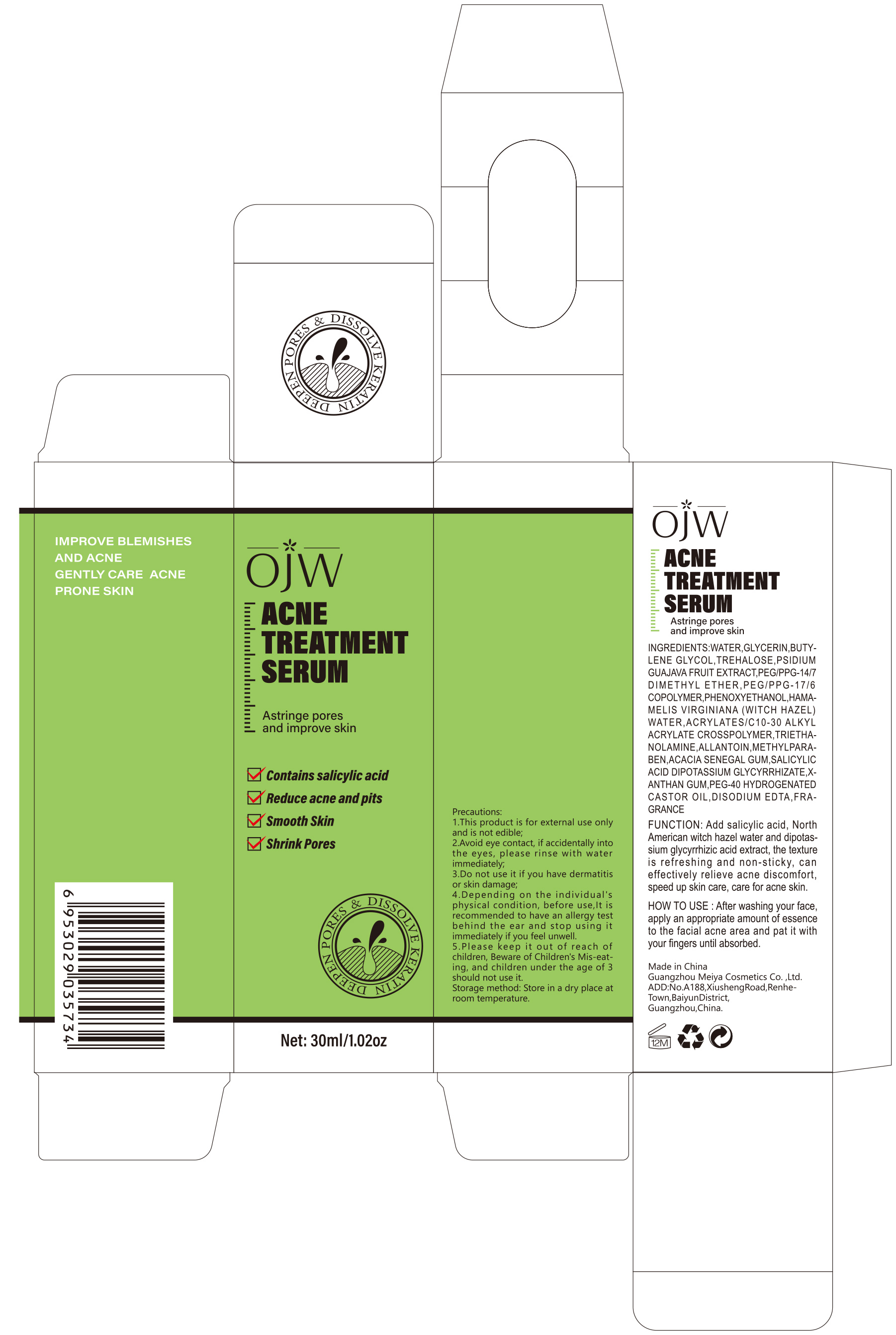 DRUG LABEL: Acne Treatment serum
NDC: 84673-005 | Form: EMULSION
Manufacturer: Guangzhou Meiya Cosmetics Co.,Ltd.
Category: otc | Type: HUMAN OTC DRUG LABEL
Date: 20240911

ACTIVE INGREDIENTS: SALICYLIC ACID 0.5 g/1 mg
INACTIVE INGREDIENTS: WATER 88.52 g/1 mg; GLYCERIN 3 g/1 mg; BUTYLENE GLYCOL 2 g/1 mg; ALLANTOIN 2 g/1 mg; XANTHAN GUM 0.1 g/1 mg; TREHALOSE 2 g/1 mg; PEG/PPG-17/6 COPOLYMER 0.5 g/1 mg; PEG/PPG-14/7 DIMETHYL ETHER 0.5 g/1 mg; PHENOXYETHANOL 0.5 g/1 mg; METHYLPARABEN 0.2 g/1 mg

ACTIVE INGREDIENT

PSIDIUM GUAJAVA FRUIT EXTRACT 5%

HAMAMELIS VIRGINIANA (WITCH HAZEL) WATER 0.5%

SALICYLIC ACID 0.3%

DIPOTASSIUM GLYCYRRHIZATE 0.28%

PURPOSE

Function: Add salicylic acid, North American witch hazel water and dipotassium glycyrrhizic acid extract, the texture is refreshing and non-sticky, can effectively relieve acne discomfort, speed up skin care, care for acne skin.

INDICATIONS AND USAGE

HOW TO USE : After washing your face, apply an appropriate amount of essence to the facial acne area and pat it with your fingers until absorbed.

WARNINGS

1. This product is for external use only and is not edible;

2. Avoid eye contact, if accidentally into the eyes, please rinse with water immediately;

3. Do not use it if you have dermatitis or skin damage;

4. Depending on the individual's physical condition, before use,It is recommended to have an allergy test behind the ear and stop using it immediately if you feel unwell.

5. Please keep it out of reach of children, Beware of Children's Mis-eating, and children under the age of 3 should not use it.

STOP USE

1. Avoid eye contact, if accidentally into the eyes, please rinse with water immediately;

2. Do not use it if you have dermatitis or skin damage;

3. Depending on the individual's physical condition, before use,It is recommended to have an allergy test behind the ear and stop using it immediately if you feel unwell.

DO NOT USE

1.This product is for external use only and is not edible;

2. Avoid eye contact, if accidentally into the eyes, please rinse with water immediately;

3.Do not use it if you have dermatitis or skin damage;

KEEP OUT OF REACH OF CHILDREN

Please keep it out of reach of children, Beware of Children's Mis-eating, and children under the age of 3 should not use it.

WHEN USING

1. This product is for external use only and is not edible;

2. Avoid eye contact, if accidentally into the eyes, please rinse with water immediately;

DOSAGE AND ADMINISTRATION

After washing your face, apply an appropriate amount of essence to the facial acne area and pat it with your fingers until absorbed.

DOSAGE AND ADMINISTRATION

After washing your face, apply an appropriate amount of essence to the facial acne area and pat it with your fingers until absorbed.